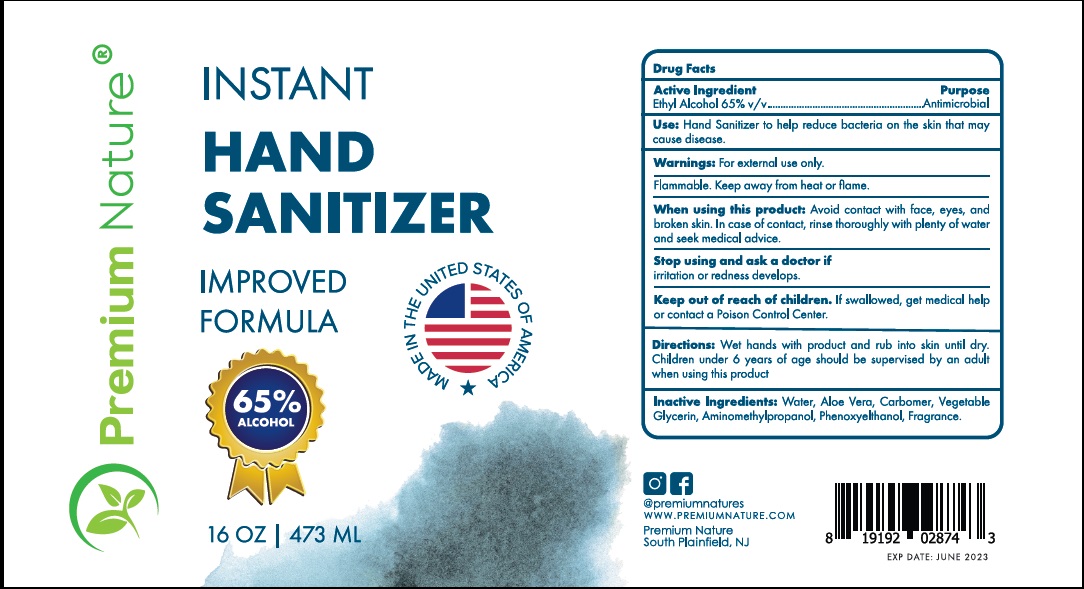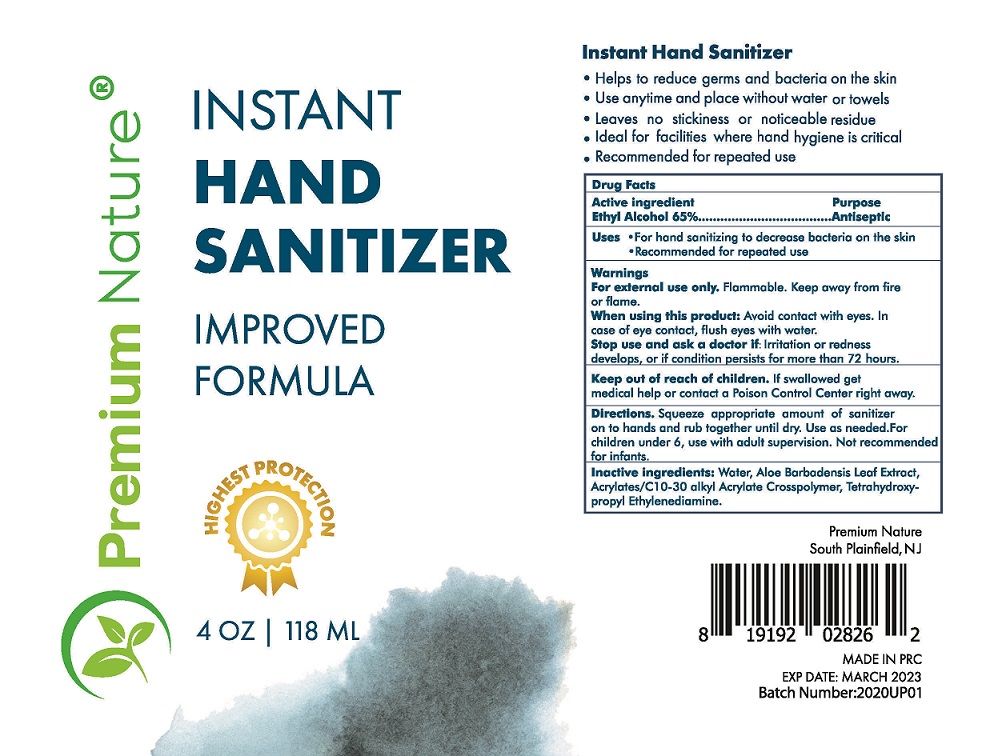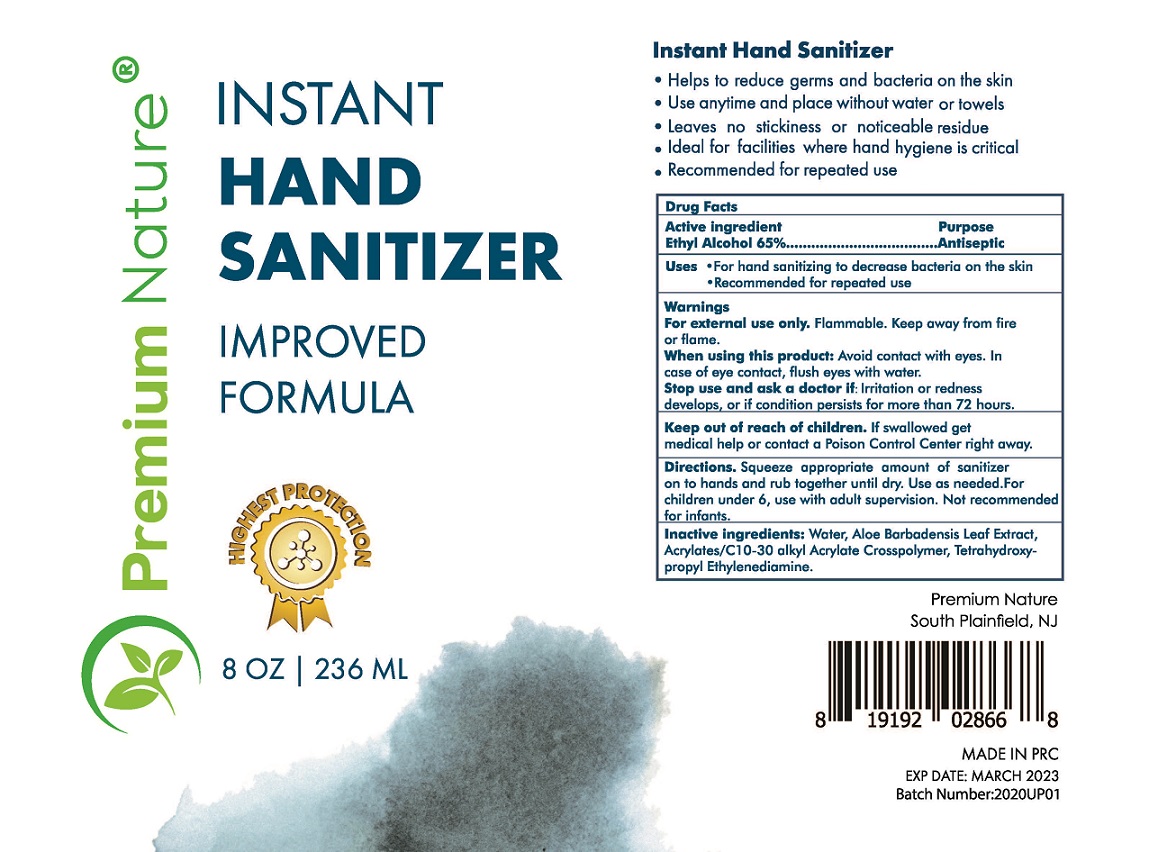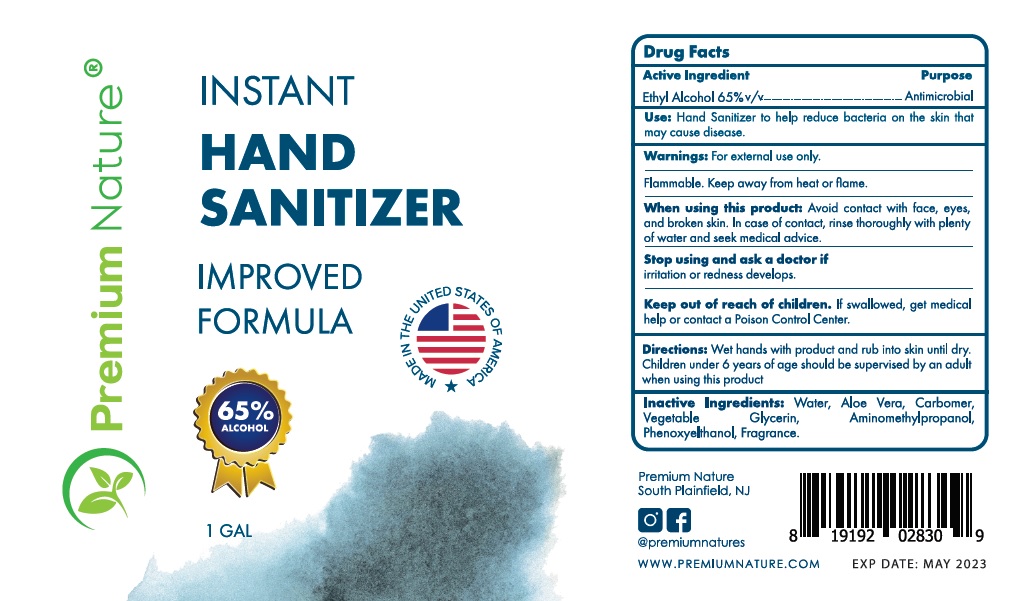 DRUG LABEL: Premium Nature Instant hand sanitizer
NDC: 75821-001 | Form: GEL
Manufacturer: Premium Assure Inc
Category: otc | Type: HUMAN OTC DRUG LABEL
Date: 20210205

ACTIVE INGREDIENTS: ALCOHOL 65 mL/100 mL
INACTIVE INGREDIENTS: EDETOL; ALOE VERA LEAF; WATER; CARBOMER INTERPOLYMER TYPE A (55000 CPS)

ACTIVE INGREDIENT

Ethyl Alcohol 65%

PURPOSE

Antiseptic hand sanitizer

USES

For hand sanitizing to decrease bacteria on skin

Recommended for repeated use

WARNINGS

For external use only. Flammable. Keep away from fire or flame.

When using this product: Avoid contact with eyes.In case of eye contact, flush eyes with water.

Stop use and ask a doctor if: irritation or redness develops,or if condition persists for more than 72 hours.

KEEP OUT OF REACH OF CHILDREN

If swallowed get medical help or contact a Poison Control Center right away.

DIRECTIONS

Squeeze appropriate amount of sanitizer on to hands and rub together until dry.

Use as needed. For children under 6, use with adult supervision. Not recommended for infants.

INACTIVE INGREDIENTS

ALOE BARBADENSIS LEAF EXTRACT, WATER, ACRYLATES/C10-30 ALKYL ACRYLATE CROSSPOLYMER,TETRAHYDROXYPROPYL ETHYLENEDIAMINE

PACKAGE LABEL - PRINCIPAL DISPLAY PANEL

118mL NDC: 75821-001-01

236mL NDC: 75821-001-02